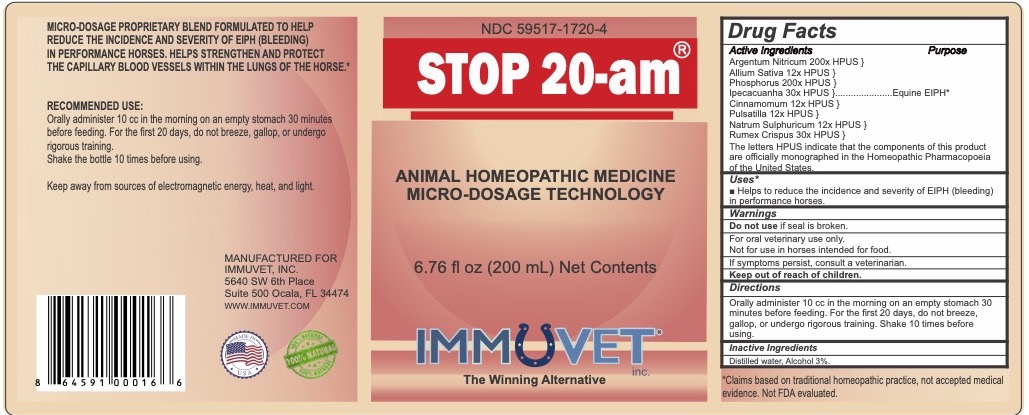 DRUG LABEL: Stop 20-am
NDC: 59517-1720 | Form: LIQUID
Manufacturer: Immuvet, Inc.
Category: homeopathic | Type: OTC ANIMAL DRUG LABEL
Date: 20251104

ACTIVE INGREDIENTS: IPECAC 30 [hp_X]/1 mL; SODIUM SULFATE 60 [hp_X]/1 mL; PHOSPHORUS 200 [hp_X]/1 mL; SILVER NITRATE 200 [hp_X]/1 mL; ONION 12 [hp_X]/1 mL; CINNAMON 12 [hp_X]/1 mL; PULSATILLA VULGARIS 12 [hp_X]/1 mL; RUMEX CRISPUS ROOT 30 [hp_X]/1 mL
INACTIVE INGREDIENTS: ALCOHOL; WATER

Stop 20-am

PURPOSE

Helps to reduce the incidence and severity of EIPH (bleeding) in performance horses.

DIRECTIONS

Orally administer 10 cc in the morning on an empty stomach 30 minutes before feeding. For the first 20 days, do not breeze, gallop, or undergo rigorous training. Shake 10 times before using.

ACTIVE INGREDIENTS

Argentum Nitricum 200x HPUS
Allium Sativa 12x HPUS
Phosphorus 200x HPUS
Ipecacuanha 30x HPUS

Cinnamomum 12x HPUS }

Pulsatilla 12x HPUS
Natrum Sulphuricum 12x HPUS
Rumex Crispus 30x HPUS

INACTIVE INGREDIENTS

Distilled water, Alcohol 3%

WARNINGS

Do not use if seal is broken.
For Oral Veterinary Use Only.
Not for use in Horses intended for food.
If problems persist, contact a veterinarian.
Keep out of reach of children.

OTHER INFORMATION

Claims based on traditional homeopathic practice, not accepted medical evidence. Not FDA evaluated.